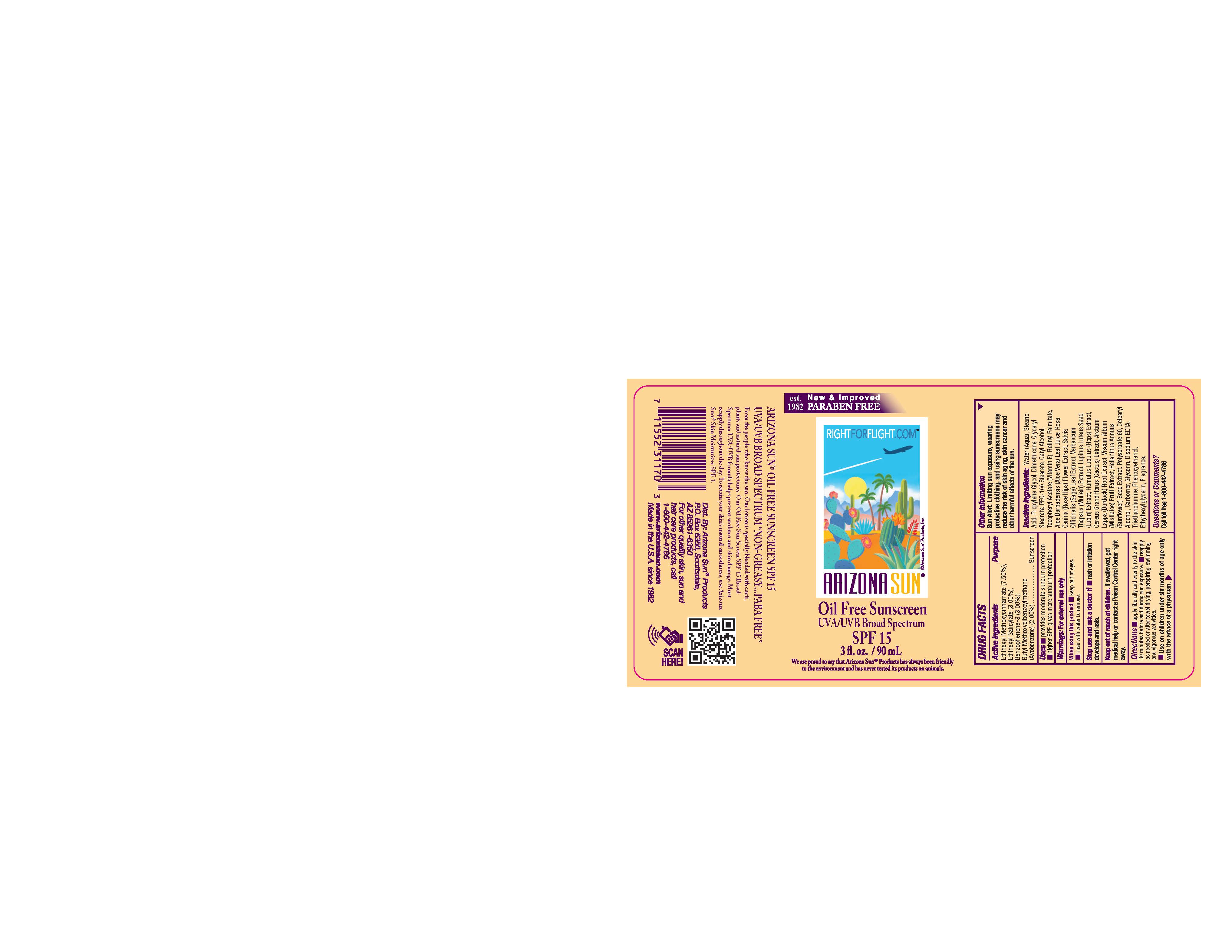 DRUG LABEL: Arizona Sun Sunscreen SPF15
NDC: 61973-101 | Form: LOTION
Manufacturer: Arizona Sun Products
Category: otc | Type: HUMAN OTC DRUG LABEL
Date: 20240207

ACTIVE INGREDIENTS: OCTISALATE 30 mg/1 g; AVOBENZONE 20 mg/1 g; OXYBENZONE 30 mg/1 g; OCTINOXATE 75 mg/1 g
INACTIVE INGREDIENTS: CETYL ALCOHOL; ROSA CANINA FLOWER; SELENICEREUS GRANDIFLORUS FLOWER; VISCUM ALBUM FRUIT; ETHYLHEXYLGLYCERIN; POLYSORBATE 60; STEARYL ALCOHOL; PHENOXYETHANOL; GLYCERYL STEARATE SE; VITAMIN A PALMITATE; PROPYLENE GLYCOL; GLYCERIN; DISODIUM EDTA-COPPER; SIMMONDSIA CHINENSIS SEED; HOPS; ARCTIUM LAPPA ROOT; TROLAMINE; DIMETHICONE; ALOE VERA LEAF; SAGE; MULLEIN LEAF; WATER; STEARIC ACID; PEG-100 STEARATE; .ALPHA.-TOCOPHEROL ACETATE; LUPINUS LUTEUS SEED; SUNFLOWER SEED; CARBOMER HOMOPOLYMER, UNSPECIFIED TYPE

3 oz Arizona Sun Sunscreen SPF 15

Active Ingredients

Ethylhexyl Methoxycinnamate (7.50%)

Ethylhexyl Salicylate (3.00%)

Benzophenone-3 (3.00%)

Butyl Methoxydibenzoylmethane (Avobenzone) (2.00%)

Purpose

Sunscreen

Uses

Provides minimal sunburn protection. Higher SPF gives more sunburn protection.

Warnings

For external use only.

When using this product

Keep out of eyes. Rinse with water to remove.

Stop and ask a doctor if

rash or irritation develops and lasts.

Keep out ot the reach of children.

If swallowed get medical help or contact a poison control center right away.

Directions

Apply liberally and evenly to the skin 30 minutes before and during sun exposure. Reapply as needed or after towel drying, perspiring, swimming, and vigorous activities. Use on children under six months of age only wih the advise of a physician.

Other Information

Sun Alert: Limiting sun exposure, wearing protective clothing, and using suscreen may reduce the risk of skin aging, skin cancer and other harmful effects of the sun.

Inactive Ingredients

Water (Agua), Stearic Acid, Propylene Glycol, Dimethicone, Glyceryl Stearate, PEG-100 Stearate, Cetyl Alcohol, Tocopheryl Acetate (Vitamin E), Retinyl Palmitate, Aloe Barbadensis (Aloe Vera) Leaf Juice, Rosa Canina (Rose Hips) Flower Extract,

Salvia Officinalis (Sage) Leaf Extract, Verbascum Thapsus (Mullein) Extract, Lupinus Luteus Seed (Lupin) Extract, Humulus Lupulus (Hops) Extract, Cereus Grandiflorus (Cactus) Extract, Arctium Lappa (Burdock) Root Extract, Viscum Album (Mistletoe) Fruit Extract, Helianthus Annuus (Sunflower) Seed Extract,

Polysorbate 60, Cetearyl Alcohol, Carbomer, Glycerin, Disodium EDTA, Triethanolamine, Phenoxyethanol, Ethylhexylglycerin, Fragrance

Questions or Comments?

Call toll free 1-800-442-4786